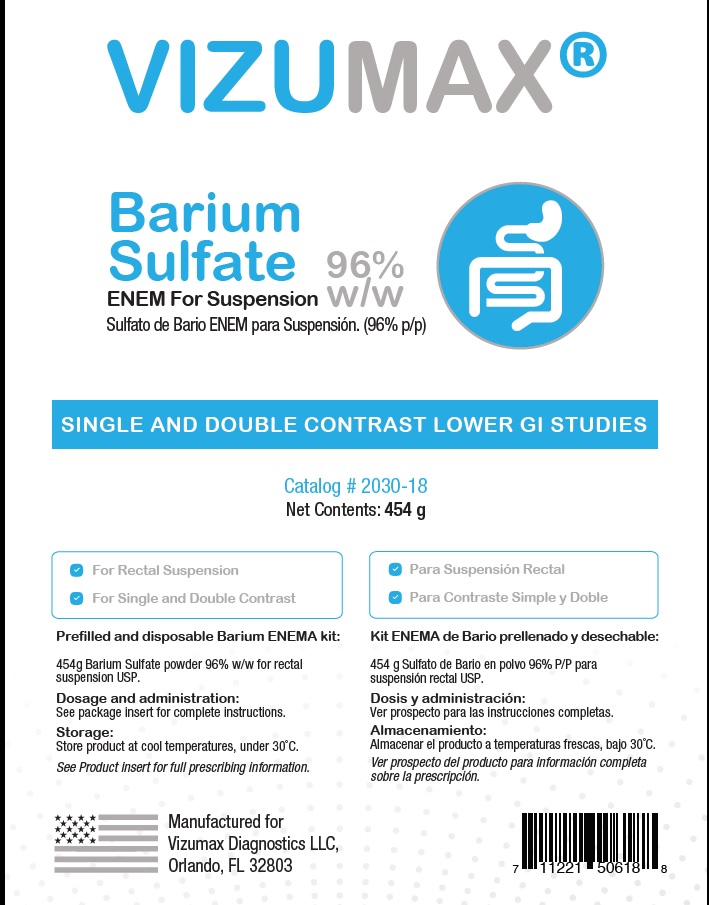 DRUG LABEL: Vizumax ENEM
NDC: 71719-2040 | Form: POWDER, FOR SUSPENSION
Manufacturer: Vizumax Diagnostics LLC
Category: prescription | Type: HUMAN PRESCRIPTION DRUG LABEL
Date: 20211004

ACTIVE INGREDIENTS: BARIUM SULFATE 960 mg/1 g
INACTIVE INGREDIENTS: SACCHARIN SODIUM ANHYDROUS; SODIUM DEHYDROACETATE; SODIUM ALGINATE; CARBOXYMETHYLCELLULOSE SODIUM; MANNITOL; SODIUM CITRATE

HIGHLIGHTS OF PRESCRIBING INFORMATION

These highlights do not include all the information needed to use, see full prescribing information for additional details.
Initial U.S. Approval.

INDICATIONS & USAGE

NDICATIONS & USAGE: Para uso como agente de contraste en estudios radiográficos.

CONTRAINDICACIONES

CONTRAINDICACIONES: Este producto no debe utilizarse en pacientes con perforación gástrica o intestinal conocida o sospechada, pacientes con afecciones que pueden aumentar el riesgo de perforación; hipersensibilidad a los productos de sulfato de bario; sospecha de fístula traqueoesofágica; lesions obstructadoras del intestino delgado; estenosis pilórica; inflamación o lesiones neoplásicas del recto; o en pacientes que han tenido una biopsia rectal reciente.
16. Las suspensiones de sulfato de bario no deben usarse en niños con trastornos de la deglución o en recién nacidos con obstrucción duodenal o yeyunal completa o cuando se sospecha obstrucción distal del intestino delgado o del colon. La suspensión de sulfato de bario no se recomienda para bebés prematuros muy pequeños y bebés pequeños que requieren pequeños volúmenes de medios de contraste o para bebés y niños pequeños cuando existe la posibilidad de fugas del tracto gastrointestinal, como enterocolitis necrotizante, neumoperitoneo inexplicable, abdomen sin gas, otros perforación intestinal, perforación esofágica o anastomosis postoperatoria.

REACCIONES ADVERSAS

REACCIONES ADVERSAS:Las reacciones adversas que acompañan el uso de formulaciones de sulfato de bario son infrecuentes y generalmente leves, aunque se han producido reacciones graves (aproximadamente 1 en 500,000) y muertes (aproximadamente 1 en 2,000,000). Las complicaciones del procedimiento son raras, pero pueden incluir neumonitis por aspiración, impactación con sulfato de bario, formación de granuloma, intravasación, embolización y peritonitis después de perforación intestinal, episodios vasovagales y sincopales y muertes. Se ha demostrado que los cambios de EKG ocurren después o durante los enemas de suspensión de sulfato de bario. Es de la mayor importancia estar completamente preparado para tratar cualquier evento de este tipo.

Debido a la mayor probabilidad de reacciones alérgicas en pacientes atópicos, un historial completo de alergias conocidas y sospechadas, así como síntomas de tipo alérgico, p. rinitis, asma bronquial, eczema y urticaria, deben obtenerse antes de cualquier procedimiento médico.

La aspiración de grandes cantidades de suspensión de sulfato de bario puede causar neumonitis o granulomas nodulares de tejidos pulmonares intersticiales y ganglios linfáticos; asfixia y muerte han sido reportadas.

La bacteriemia transitoria puede ocurrir durante la administración rectal de la suspensión de sulfato de bario, y se ha informado de septicemia.

Una reacción alérgica leve y poco común sería la prurito generalizada, el eritema o la urticaria (aproximadamente 1 de cada 100.000 reacciones). Tales reacciones a menudo responderán a un antihistamínico. Las reacciones más graves (aproximadamente 1 en 500,000) pueden causar edema laríngeo, broncoespasmo o hipotensión.

Las reacciones graves que pueden requerir medidas de emergencia a menudo se caracterizan por vasodilatación periférica, hipotensión, taquicardia refleja, disnea, broncoespasmo, agitación, confusión y cianosis, que progresa hasta la inconsciencia. El tratamiento debe iniciarse de inmediato de acuerdo con el estándar de atención establecido.

Los pacientes aprensivos pueden desarrollar debilidad, palidez, tinnitus, diaforesis y bradicardia después de la administración de cualquier agente de diagnóstico. Tales reacciones son generalmente de naturaleza no alérgica.To report suspected adverse reactions please call 1-800-332-1088

DOSIS Y ADMINISTRACIÓN: El volumen de sulfato de bario y el método de administración se determinan mediante una técnica individual, y pueden variar según las diferentes características del paciente y del procedimiento.

FULL PRESCRIBING INFORMATION

DESCRIPCIÓN

Vizumax-ENEM es un sulfato de bario para suspensión 96% p / p para administración rectal. Cada 100 g contiene 96 g de sulfato de bario. El sulfato de bario, debido a su alta densidad molecular, es opaco a los rayos X y, por lo tanto, actúa como un agente de contraste positivo para estudios radiográficos. El ingrediente activo es sulfato de bario y su fórmula estructural es BaSO4. El sulfato de bario se presenta como un polvo fino, blanco, inodoro, insípido y voluminoso, libre de arenosidad. Sus suspensiones acuosas son neutrales al tornasol. Es prácticamente insoluble en agua, soluciones de ácidos y álcalis, o solventes orgánicos.

FARMACOLOGÍA CLÍNICA

El sulfato de bario, debido a su alta densidad molecular, es opaco a los rayos X y, por lo tanto, actúa como un agente de contraste positivo para estudios radiográficos. El sulfato de bario es biológicamente inerte y, por lo tanto, no es absorbido o metabolizado por el cuerpo, y se elimina del tracto gastrointestinal sin cambios. La tasa de excreción es una función del tiempo de tránsito gastrointestinal.

INDICATIONS & USAGE

NDICATIONS & USAGE: Para uso como agente de contraste en estudios radiográficos.These highlights do not include all the information needed to use, see full prescribing information for, Initial U.S. Approval.

CONTRAINDICACIONES

CONTRAINDICACIONES: Este producto no debe utilizarse en pacientes con perforación gástrica o intestinal conocida o sospechada, pacientes con afecciones que pueden aumentar el riesgo de perforación; hipersensibilidad a los productos de sulfato de bario; sospecha de fístula traqueoesofágica; lesions obstructadoras del intestino delgado; estenosis pilórica; inflamación o lesiones neoplásicas del recto; o en pacientes que han tenido una biopsia rectal reciente.
16. Las suspensiones de sulfato de bario no deben usarse en niños con trastornos de la deglución o en recién nacidos con obstrucción duodenal o yeyunal completa o cuando se sospecha obstrucción distal del intestino delgado o del colon. La suspensión de sulfato de bario no se recomienda para bebés prematuros muy pequeños y bebés pequeños que requieren pequeños volúmenes de medios de contraste o para bebés y niños pequeños cuando existe la posibilidad de fugas del tracto gastrointestinal, como enterocolitis necrotizante, neumoperitoneo inexplicable, abdomen sin gas, otros perforación intestinal, perforación esofágica o anastomosis postoperatoria.

ADVERTENCIAS

ADVERTENCIAS: Se han notificado reacciones adversas graves, incluida la muerte, con la administración de formulaciones de sulfato de bario y generalmente están asociadas con la técnica de administración, la afección patológica subyacente y / o hipersensibilidades del paciente.

PRECAUCIONES

General: los procedimientos que implican el uso de medios de contraste radiopacos deben llevarse a cabo bajo la dirección de personal con la capacitación requerida y con un conocimiento profundo del procedimiento particular que se realizará. Los antecedentes de asma bronquial, atopia, como lo evidencian la fiebre del heno y el eccema, o una reacción previa a un agente de contraste, merecen especial atención. Se debe tener precaución con el uso de medios radiopacos en pacientes severamente debilitados y en aquellos con hipertensión marcada o enfermedad cardiaca avanzada. No se recomienda la ingestión de bario en pacientes con antecedentes de aspiración de alimentos. Tenga cuidado si administra este producto a pacientes en quienes se desconoce la integridad del mecanismo de deglución. Si se aspira bario en la laringe, se debe interrumpir inmediatamente la administración posterior. Después de cualquier estudio con bario del tracto gastrointestinal, puede ser importante rehidratar al paciente lo más rápido posible para evitar la impactación del bario. Para evitar la impactación del bario en el colon, también puede ser necesario el uso de laxantes suaves como leche de magnesia o lactulosa después de la finalización del examen. Estos laxantes suaves se recomiendan de forma rutinaria y en pacientes con antecedentes de estreñimiento a menos que esté clínicamente contraindicado.

REACCIONES ADVERSAS

REACCIONES ADVERSAS:Las reacciones adversas que acompañan el uso de formulaciones de sulfato de bario son infrecuentes y generalmente leves, aunque se han producido reacciones graves (aproximadamente 1 en 500,000) y muertes (aproximadamente 1 en 2,000,000). Las complicaciones del procedimiento son raras, pero pueden incluir neumonitis por aspiración, impactación con sulfato de bario, formación de granuloma, intravasación, embolización y peritonitis después de perforación intestinal, episodios vasovagales y sincopales y muertes. Se ha demostrado que los cambios de EKG ocurren después o durante los enemas de suspensión de sulfato de bario. Es de la mayor importancia estar completamente preparado para tratar cualquier evento de este tipo.

Debido a la mayor probabilidad de reacciones alérgicas en pacientes atópicos, un historial completo de alergias conocidas y sospechadas, así como síntomas de tipo alérgico, p. rinitis, asma bronquial, eczema y urticaria, deben obtenerse antes de cualquier procedimiento médico.

La aspiración de grandes cantidades de suspensión de sulfato de bario puede causar neumonitis o granulomas nodulares de tejidos pulmonares intersticiales y ganglios linfáticos; asfixia y muerte han sido reportadas.

La bacteriemia transitoria puede ocurrir durante la administración rectal de la suspensión de sulfato de bario, y se ha informado de septicemia.

Una reacción alérgica leve y poco común sería la prurito generalizada, el eritema o la urticaria (aproximadamente 1 de cada 100.000 reacciones). Tales reacciones a menudo responderán a un antihistamínico. Las reacciones más graves (aproximadamente 1 en 500,000) pueden causar edema laríngeo, broncoespasmo o hipotensión.

Las reacciones graves que pueden requerir medidas de emergencia a menudo se caracterizan por vasodilatación periférica, hipotensión, taquicardia refleja, disnea, broncoespasmo, agitación, confusión y cianosis, que progresa hasta la inconsciencia. El tratamiento debe iniciarse de inmediato de acuerdo con el estándar de atención establecido.

Los pacientes aprensivos pueden desarrollar debilidad, palidez, tinnitus, diaforesis y bradicardia después de la administración de cualquier agente de diagnóstico. Tales reacciones son generalmente de naturaleza no alérgica.

DOSIS Y ADMINISTRACIÓN: El volumen de sulfato de bario y el método de administración se determinan mediante una técnica individual, y pueden variar según las diferentes características del paciente y del procedimiento. Añadir 65 ml de agua para crear una suspensión de 135 ml con una densidad del 250% p / v (85% p / p). Vuelva a coloquar tapa de forma segura. Invertir la botella y toque con la mano el fondo para aflojar el polvo. Agitar vigorosamente durante 30 segundos y deje reposar al durants 5 minutos. Agregue agua adicional según sea necesario para lograr la% de mezcla deseada. Vuelva a colocar la tapa y agitar nuevamente durante 30 segundos.

ALMACENAMIENTO

Almacener el producto a menos de 30 ° C.